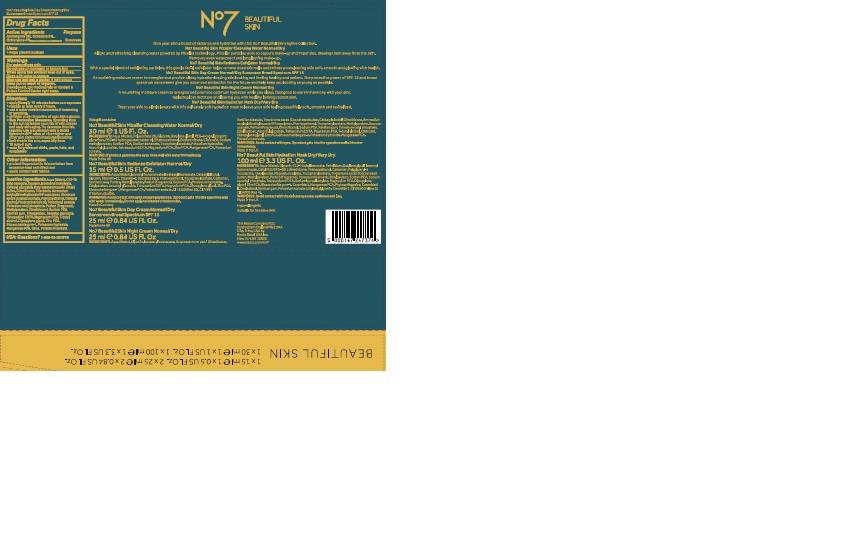 DRUG LABEL: No7 Beautiful Skin Day Cream  Normal Dry SPF 15
NDC: 11489-116 | Form: CREAM
Manufacturer: BCM Ltd
Category: otc | Type: HUMAN OTC DRUG LABEL
Date: 20170707

ACTIVE INGREDIENTS: AVOBENZONE 0.75 g/25 g; OCTOCRYLENE 1 g/25 g; OCTISALATE 0.5 g/25 g
INACTIVE INGREDIENTS: WATER; GLYCERIN; ALKYL (C12-15) BENZOATE; DIMETHICONE; ISOSTEARYL ISOSTEARATE; CETEARYL GLUCOSIDE; ALUMINUM STARCH OCTENYLSUCCINATE; TRIBEHENIN; POTASSIUM CETYL PHOSPHATE; AMMONIUM ACRYLOYLDIMETHYLTAURATE/VP COPOLYMER; PHENOXYETHANOL; CETOSTEARYL ALCOHOL; SHEA BUTTER; METHYLPARABEN; DIMETHICONOL (40 CST); ETHYLPARABEN; DIPROPYLENE GLYCOL; XANTHAN GUM; ASCORBYL GLUCOSIDE; EDETATE SODIUM; BIOSACCHARIDE GUM-1; TERT-BUTYL ALCOHOL; POTASSIUM HYDROXIDE; MANGANESE PCA; POTASSIUM SORBATE; ROSA CANINA FRUIT OIL

No7 Beautiful Skin Day Cream Normal Dry Sunscreen Broad Spectrum SPF 15

Carton Active Ingredients Section

Active ingredients

Avobenzone 3%

Octisalate 2%

Octocrylene 4%

Uses

Uses - helps prevent sunburn

Warnings

For external use only

Do not use on damaged or broken skin

When using this product keep out of eyes. Rinse with water to remove.

Ask a doctor

Stop use and ask a doctor if rash occurs

Keep out of reach of children

If swallowed, get medical help or contact a Poison Control Center right away

Directions

Apply liberally 15 minutes before sun exposure

reapply at least every 2 hours

use a water resistant sunscreen if swimming or sweating

children under 6 months of age: Ask a doctor

Sun Protection Measures. Spending time in the sun increases your risk of skin cancer and early skin aging.

To decrease this risk, regularly use a sunscreen with a Broad Spectrum SPF value of 15 or higher and other sun protection measures including:

Limit time in the sun, especially from 10 a.m - 2 p.m.

wear long-sleeved shirts,pants,hats and sunglasses.

Storage

Other information

Protect the product in this container from excessive heat and direct sun

Avoid contact with fabrics

Inactive ingredients

Aqua(Water), Glycerin, C12-15 alkyl bezoate, Isostearyl isostearate, Dimethicone, Cetearyl glucoside, Aluminum starch octenylsuccinate, Tribehenin, Ammonium acryloydimethyltaurate/VP copolymer, Phenoxyethanol, Butyrospermum parkii (Shea) butter, Potassium cetyl phosphate, Tocopheryl acetate, Rosa canina fruit oil, Cetearyl alcohol, Dimethiconol, Sodium PCA, Methyparaben, Parfum(Fragrance) Xanthan gum, Ethylparaben, Dipropylene glycol, Ascorbyl glucoside, Tetrasodium EDTA, Magnesium PCA, T-butyl alcohol, Zinc PCA, Biosaccharide gum-1, Potassium hydroxide, Manganese PCA, Silica, Potassium sorbate.

PATIENT COUNSELING INFORMATION

Made in the UK

The Boots Company PLC Nottingham England NG2 3AA

Dist. by Boots Retail USA Inc. New York NY 10005

www.boots.com

Description

No7 Beautiful Skin

Give your skin a boost of radiance and hydration with this No7 Beautiful Skin regime collection.

No7 Beautiful Skin Micellar Cleansing Water Normal/Dry

A light and refreshing cleansing water powered by Micellar technology. Micellar particles work to capture make-up and impurities,drawing them away from the skin. Removes even waterproof and long lasting make-up.

No7 Beautiful Skin Radiance Exfoliator Norma/Dry

With a special blend of exfoliating particles, this gentle facial exfoliator helps remove dead skin cellls and refines pores, leaving skin soft, smooth and glowing with health.

No7 Beautiful Skin Day Cream NormalDry Sunscreen Broad Spectrum SPF 15

A nourishing moisture cream to energise and provide all day hydration leaving skin looking and feeling healthy and radiant. The protective power of SPF 15 and broad spectrum sunscreens give you advanced protection for the future and help keep you looking as young as possible.

No7 Beautiful Skin Night Cream Normal/Dry

A nourishing moisture cream to energise and promote optimum hydration while you sleep. Designed to work in harmony with your skin, replacing lost moisture and leaving you with healthy looking radiant skin.

No7 Beautiful Skin Hydration Mask Dry/Very Dry

Treta your skin to a little luxury with this delicately soft hydration mask to leave your skin feeling beautifully soft, smooth and revitalized